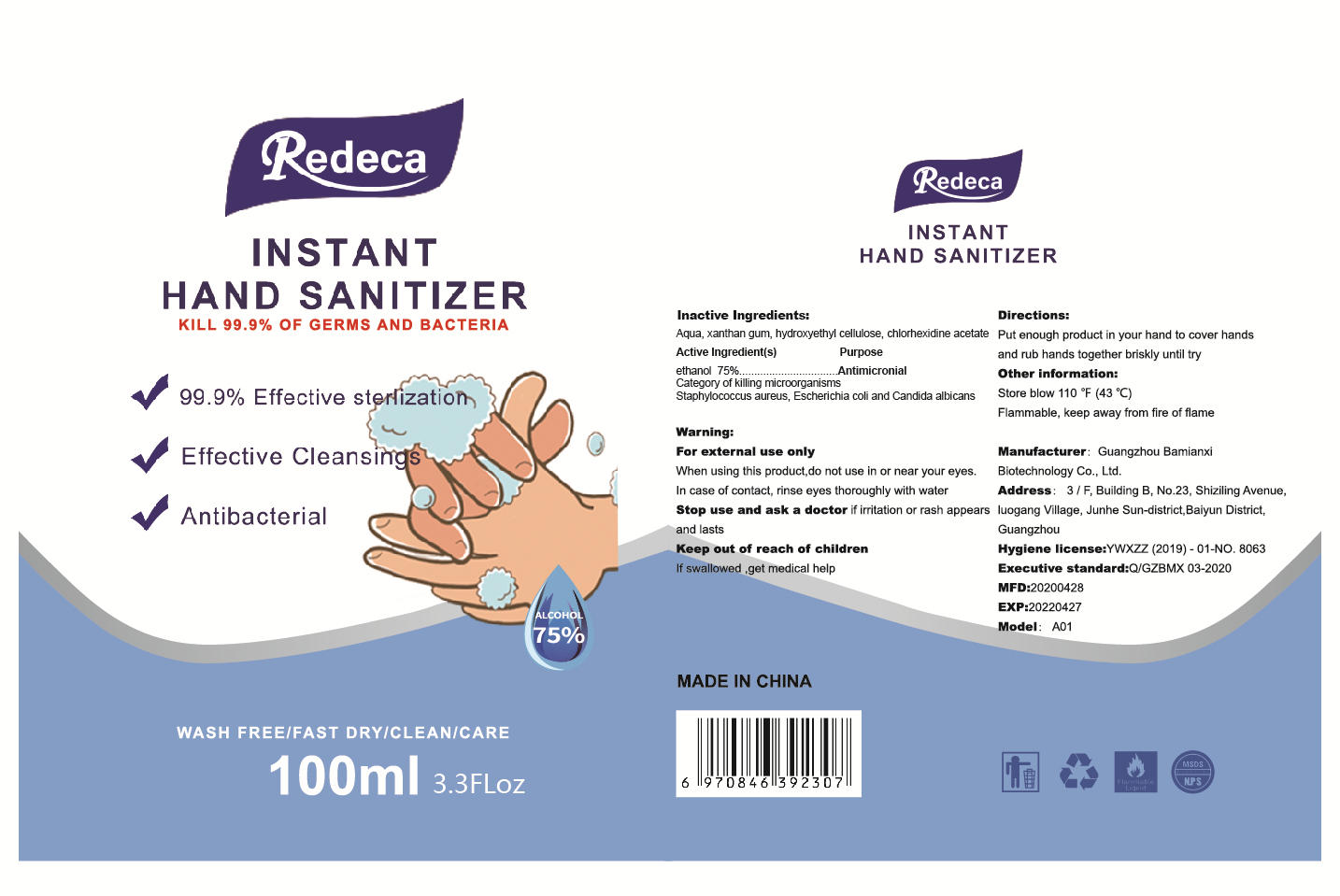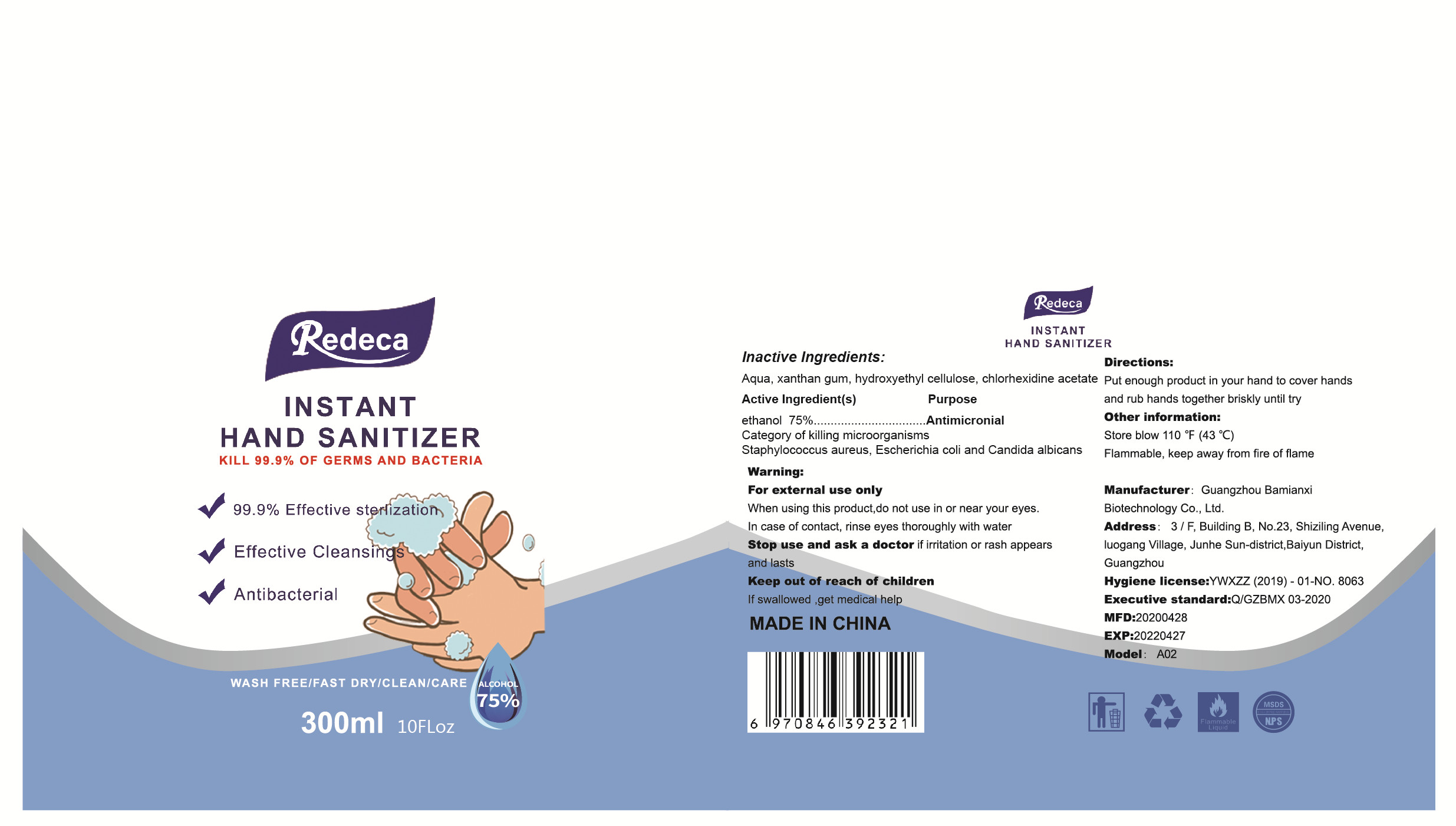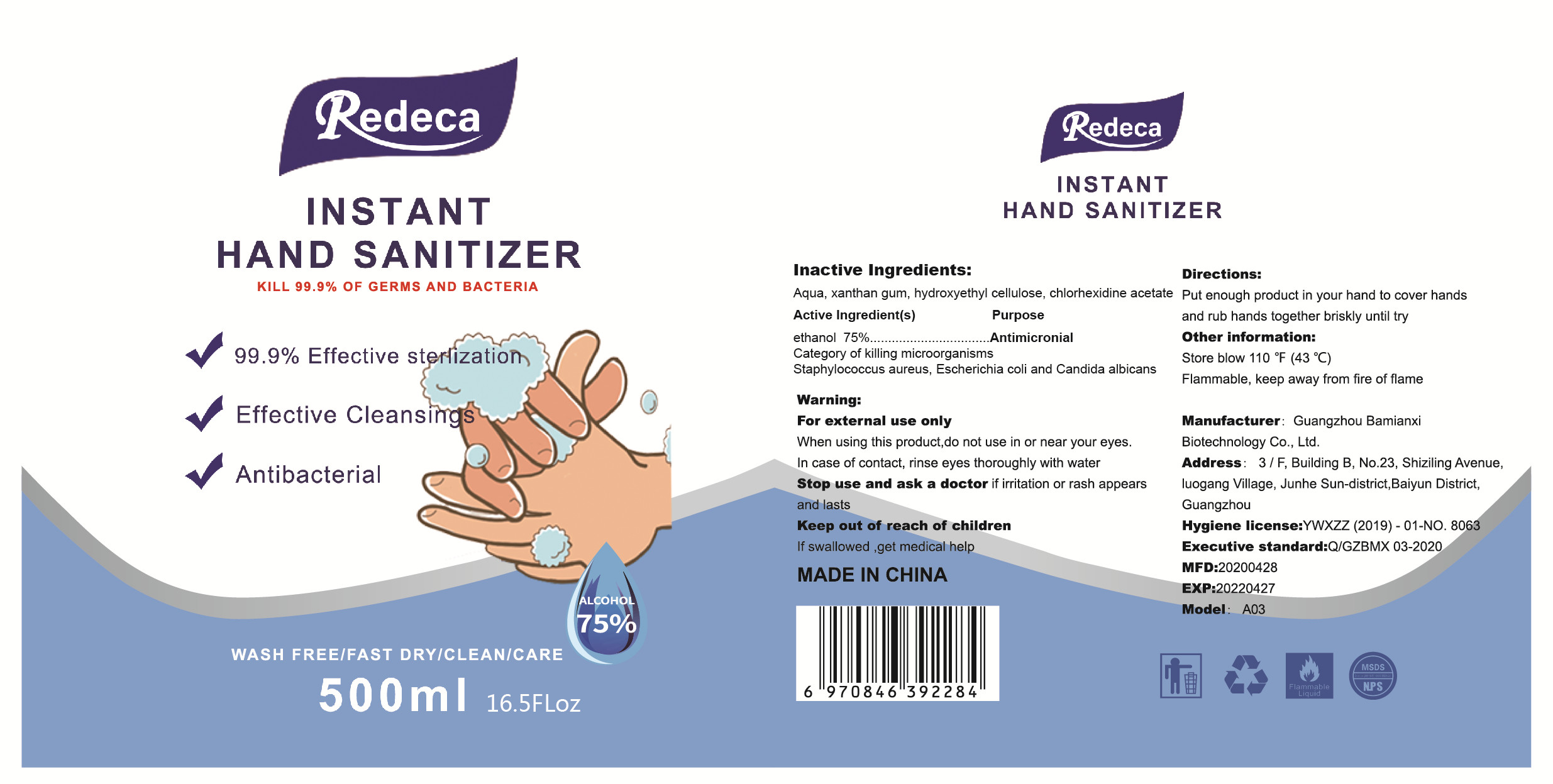 DRUG LABEL: INSTANT HAND SANITIZER
NDC: 78223-007 | Form: GEL
Manufacturer: Guangzhou Bamianxi Biotechnology Co., Ltd
Category: otc | Type: HUMAN OTC DRUG LABEL
Date: 20200722

ACTIVE INGREDIENTS: ALCOHOL 75 mL/100 mL
INACTIVE INGREDIENTS: XANTHAN GUM; CHLORHEXIDINE ACETATE; HYDROXYETHYL CELLULOSE (2000 CPS AT 1%); WATER

007

Active Ingredient(s)

Ethanol 75% v/v. Purpose: Antiseptic

Purpose

Antimicronial

Use

Hand Sanitizer to help reduce bacteria that potentially can cause disease. For use when soap and water arenot available

Warnings

For external use only

When using this product do not use in or near your eyIn case of contact, rinse eyes thoroughly with water

Stop use and ask a doctor f irritation or rash appearsand asts

Keep out of reach of childrenIf swallowed get medical help

Do not use

/

When using this product, do not use in or near your eyes In case of contact, rinse eyes thoroughly with water

Stop use and ask a doctor f irritation or rash appeaand lasts

KEEP OUT OF REACH OF CHILDREN

Keep out of reach of childrenIf swallowed, get medical help

Directions

- Put enough product in your hand to cover hands and rub hands together briskly until try

Other information

- Other information:Store blow110F(43℃Flammable, keep away from fire of flame

Inactive ingredients

Aqua, xanthan gum, hydroxyethyl cellulose, chlorhexidine acetate